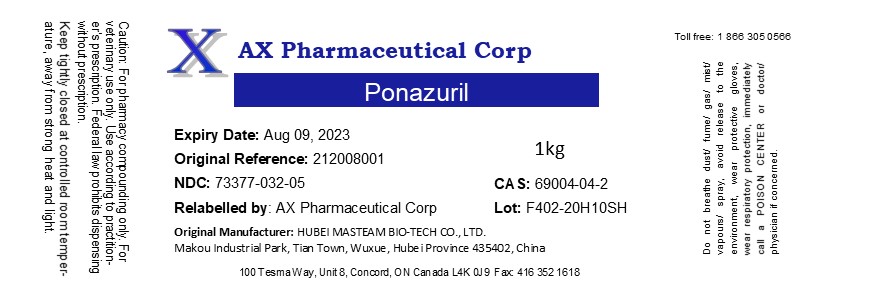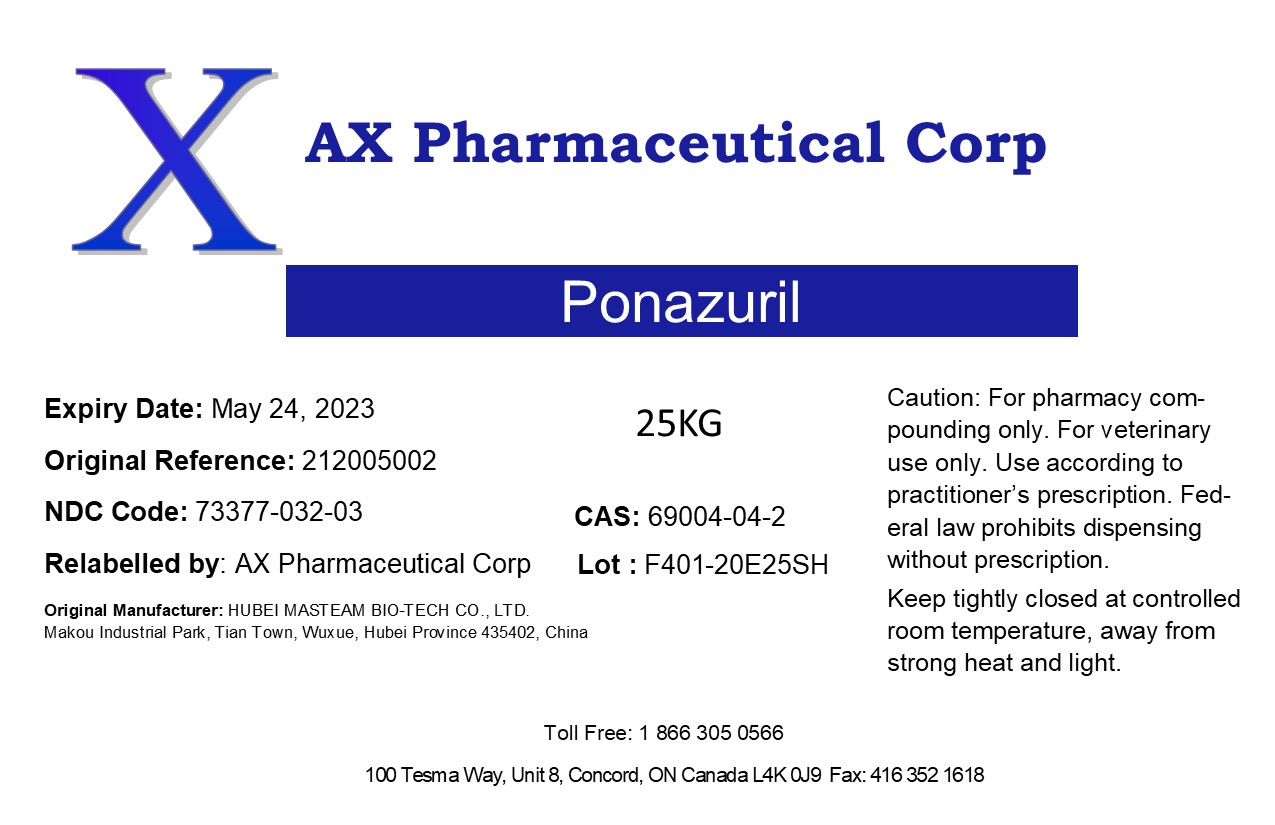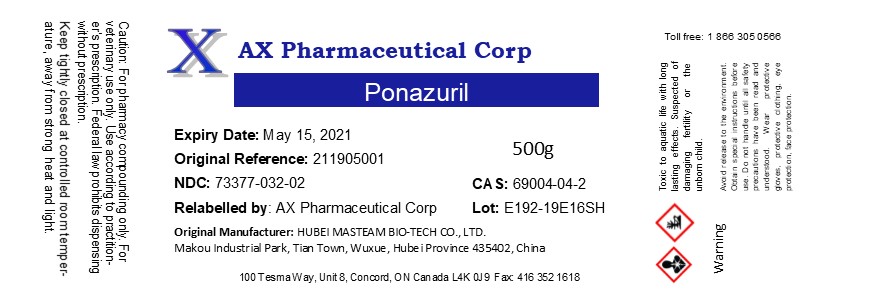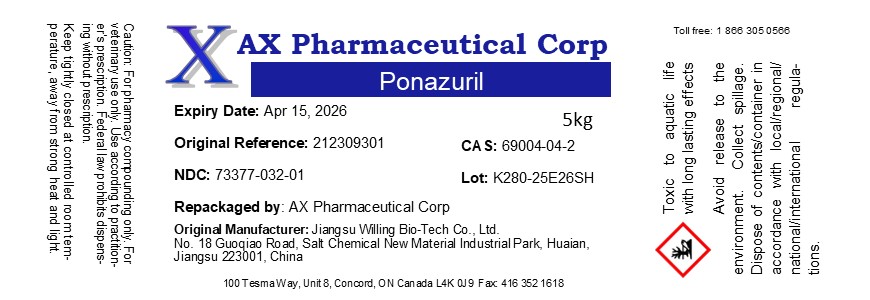 DRUG LABEL: Ponazuril
NDC: 73377-032 | Form: POWDER
Manufacturer: AX Pharmaceutical Corp
Category: other | Type: BULK INGREDIENT - ANIMAL DRUG
Date: 20260116

ACTIVE INGREDIENTS: PONAZURIL 1 kg/1 kg

Ponazuril